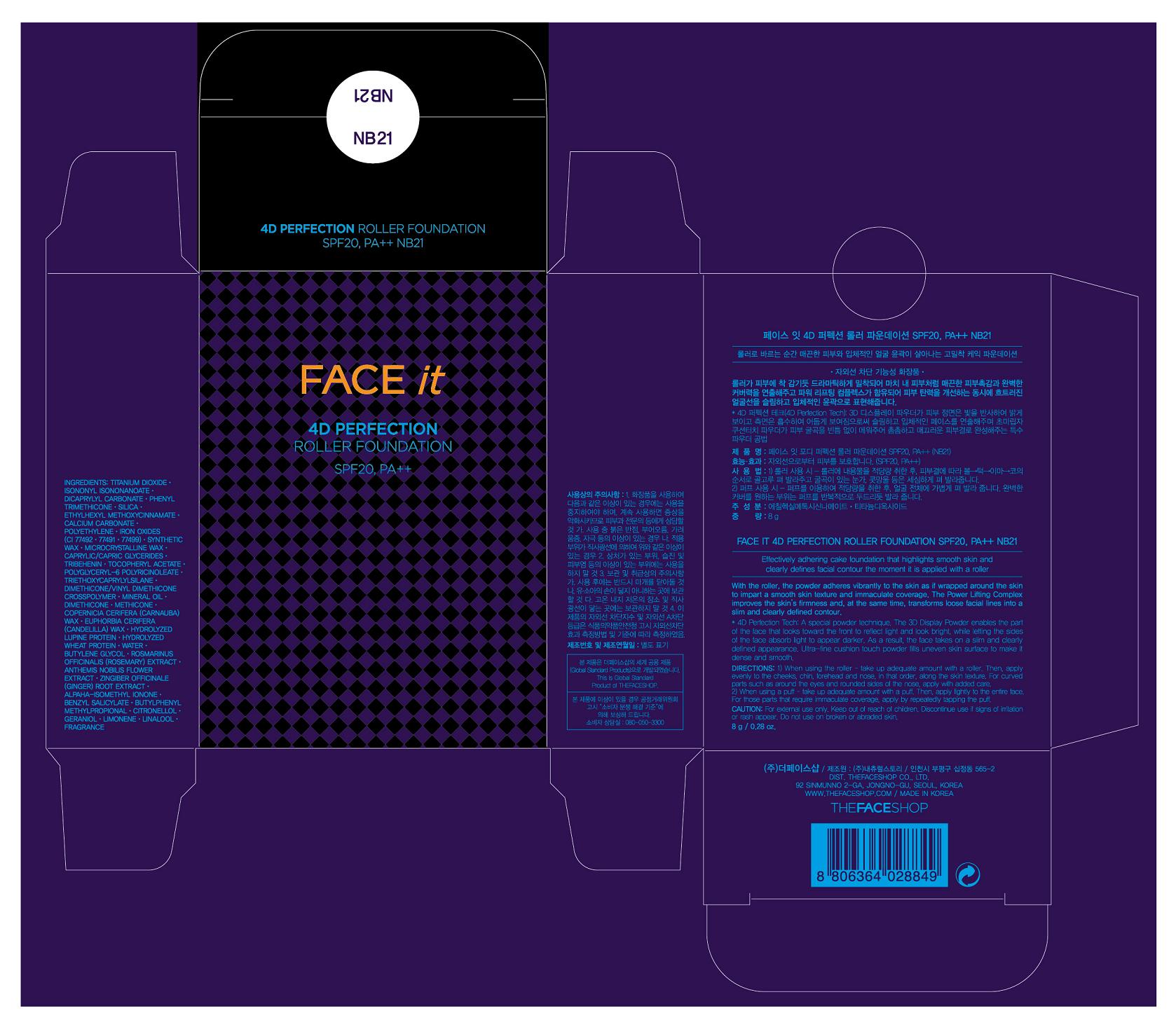 DRUG LABEL: FACE IT 4D PERFECTION ROLLER  FOUNDATION 21
NDC: 51523-109 | Form: CREAM
Manufacturer: THEFACESHOP CO., LTD
Category: otc | Type: HUMAN OTC DRUG LABEL
Date: 20110901

ACTIVE INGREDIENTS: OCTINOXATE 3 g/100 g; TITANIUM DIOXIDE 23.51 g/100 g
INACTIVE INGREDIENTS: WATER; TRIETHOXYCAPRYLYLSILANE; ISONONYL ISONONANOATE; DICAPRYLYL CARBONATE; PHENYL TRIMETHICONE; DIMETHICONE; SILICON DIOXIDE; MINERAL OIL; CALCIUM CARBONATE; HIGH DENSITY POLYETHYLENE; FERRIC OXIDE RED; CARNAUBA WAX; CANDELILLA WAX; MICROCRYSTALLINE WAX; TRIBEHENIN; HYDROLYZED WHEAT PROTEIN (ENZYMATIC, 3000 MW); BUTYLENE GLYCOL; CHAMAEMELUM NOBILE FLOWER; GINGER

Drug Facts

ACTIVE INGREDIENT

OCTINOXATE (3%)
TITANIUM DIOXIDE (23.51%)

INACTIVE INGREDIENT

TRIETHOXYCAPRYLYLSILANE
WATER
ISONONYL ISONONANOATE
DICAPRYLYL CARBONATE
PHENYL TRIMETHICONE
DIMETHICONE
SILICON DIOXIDE
MINERAL OIL
CALCIUM CARBONATE
HIGH DENSITY POLYETHYLENE
FERRIC OXIDE RED
CARNAUBA WAX
CANDELILLA WAX
MICROCRYSTALLINE WAX
TRIBEHENIN
HYDROLYZED WHEAT PROTEIN (ENZYMATIC, 3000 MW)
BUTYLENE GLYCOL
CHAMAEMELUM NOBILE FLOWER
GINGER

PURPOSE

Provides high protection against sunburn and tanning.

WHEN USING

Avoid contact with eyes.

STOP USE

Discontinue use if sign of irritation or rash appear.

DOSAGE AND ADMINISTRATION

Dispense an adequate amount and apply evenly. (At the final stage of basic skincare, dispense an adequate amount and apply evenly to desired parts)

PACKAGE LABEL

FACE IT 4D PERFECTION ROLLER FOUNDATION NB 21